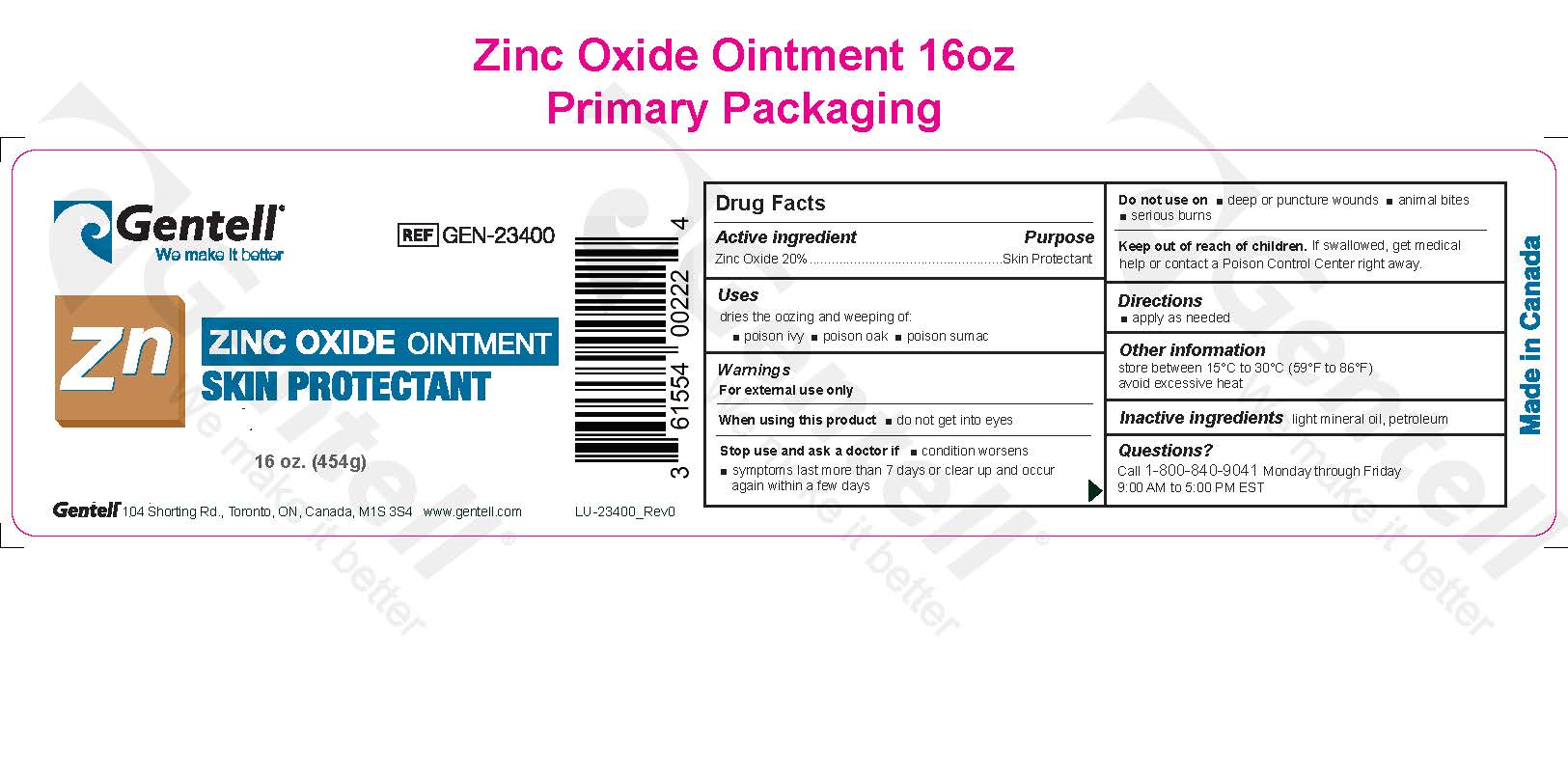 DRUG LABEL: Zinc Oxide
NDC: 64772-201 | Form: OINTMENT
Manufacturer: Derma Sciences Canada Inc.
Category: otc | Type: HUMAN OTC DRUG LABEL
Date: 20250619

ACTIVE INGREDIENTS: ZINC OXIDE 0.2 g/1 g
INACTIVE INGREDIENTS: PETROLATUM 0.75 g/1 g; LIGHT MINERAL OIL 0.05 g/1 g

ACTIVE INGREDIENT

Zinc Oxide 20%

When using this product

- do not get into eyes

INACTIVE INGREDIENT

light mineral oil, petrolatum

Do not use on

- deep puncture wounds
- animal bites
- serious burns

PURPOSE

Skin Protectant

Warnings

For external use only

When using this product

■ do not get into eyes

Stop use and ask a doctor if

■ condition worsens

■ symptoms last more than 7 days or clear up and occur again within a few days

Do not use on

■ deep or puncture wounds ■ animal bites ■ serious burns

Keep out of reach of children. If swallowed, get medical help or contact a Poison Control Center right away.

Keep out of reach of children. If swallowed, get medical help or contact a Poison Control Center right away.

Questions?

Call 800-840-9041 Monday through Friday 9:00 AM to 5:00 PM EST

Other Information

store between 15ºC to 30ºC (59ºF to 86ºF)

avoid excessive heat

Directions

- apply as needed

Uses

dries the oozing and weeping of:

■ poison ivy ■ poison oak ■ poison sumac

Stop use and ask a doctor if ■ condition worsens ■ symptoms last more than 7 days or clear up and occur again within a few days

Stop use and ask a doctor if ■ condition worsens ■ symptoms last more than 7 days or clear up and occur again within a few days